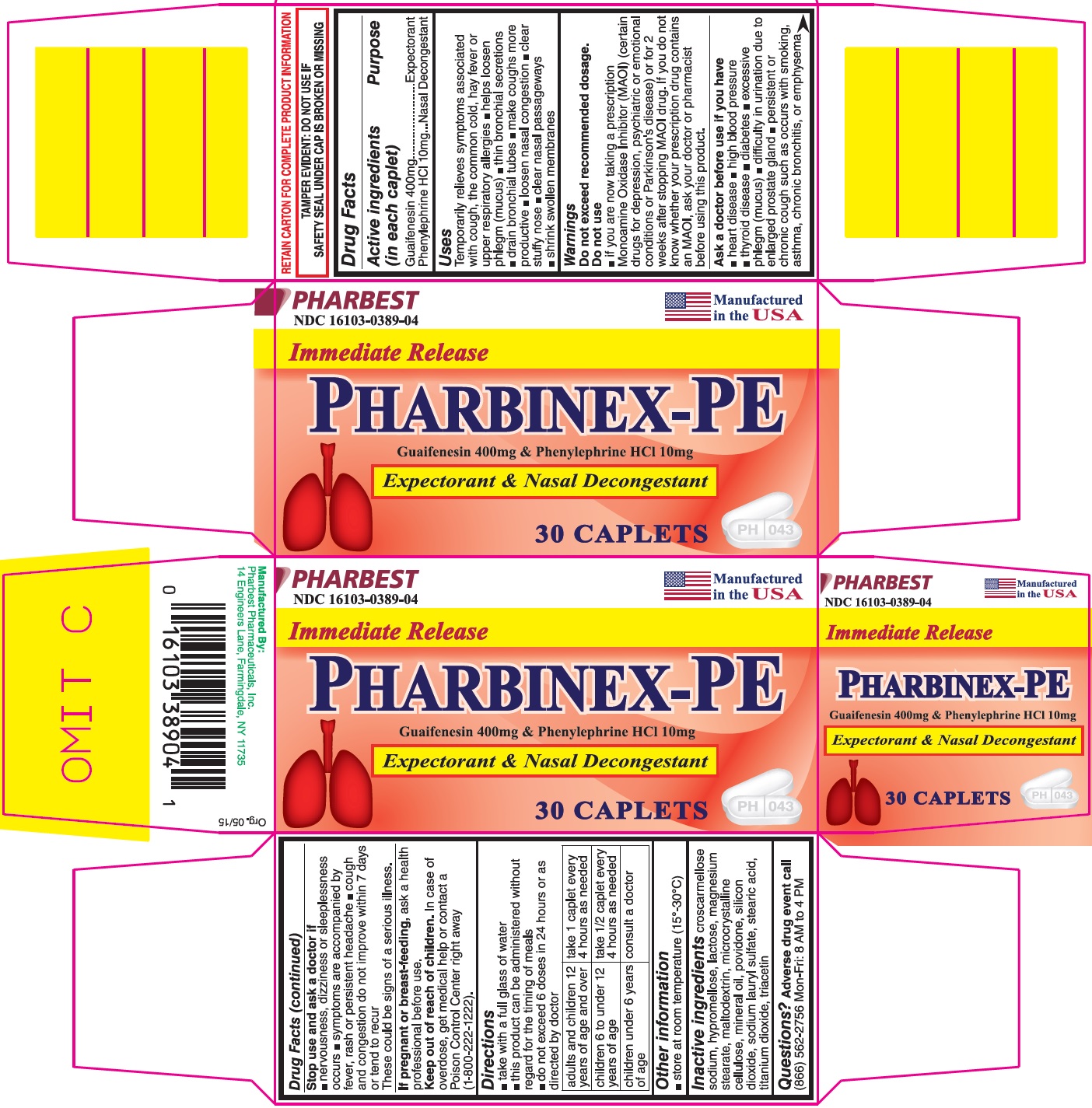 DRUG LABEL: PHARBINEX-PE
NDC: 16103-389 | Form: TABLET, COATED
Manufacturer: Pharbest Pharmaceuticals, Inc.
Category: otc | Type: HUMAN OTC DRUG LABEL
Date: 20180501

ACTIVE INGREDIENTS: GUAIFENESIN 400 mg/1 1; PHENYLEPHRINE HYDROCHLORIDE 10 mg/1 1
INACTIVE INGREDIENTS: CROSCARMELLOSE SODIUM; HYPROMELLOSE, UNSPECIFIED; LACTOSE MONOHYDRATE; MAGNESIUM STEARATE; MALTODEXTRIN; CELLULOSE, MICROCRYSTALLINE; MINERAL OIL; POVIDONE, UNSPECIFIED; SILICON DIOXIDE; SODIUM LAURYL SULFATE; STEARIC ACID; TITANIUM DIOXIDE; TRIACETIN

Drug Facts

Active ingredients (in each caplet)

Guaifenesin 400mg

Phenylephrine HCl 10mg

Purpose

Expectorant

Nasal Decongestant

Uses

Temporarily relieves symptoms associated with cough, the common cold, hay fever or upper respiratory allergies

- helps loosen phlegm(mucus)
- thin bronchial secretions
- drain bronchial tubes
- make coughs more productive
- loosen nasal congestion
- clear stuffy nose
- clear nasal passageways
- shrinks swollen membranes

Warnings

Do not exceed recommended dosage.

Do not use

- if you are now taking a prescription Monoamine Oxidase Inhibitor (MAOI)(certain drugs for depression, psychiatric or emotional conditions or Parkinson's disease) or for 2 weeks after stopping MAOI drug. If you do not know whether your prescription drug contains an MAOI, ask your doctor or pharmacist before using this product.

Ask a doctor before use if you have

- heart disease
- high blood pressure
- thyroid disease
- diabetes
- excessive phlegm (mucus)
- difficulty in urination due to enlargement of prostate gland
- persistent or chronic cough such as occurs with smoking, asthma, chronic bronchitis, or emphysema

Stop use and ask a doctor if

- nervousness, dizziness or sleeplessness occurs
- symptoms are accompanied by fever, rash or persistent headache
- cough and congestion do not improve within 7 days or tend to recur

These could be signs of a serious illness.

If pregnant or breast-feeding,

ask a health professional before use.

Keep out of reach of children.

In case of overdose, get medical help or contact a Poison Control Center right away (1-800-222-1222).

Directions

- take with a full glass of water
- this product can be administered without regard for the timing of meals
- do not exceed 6 doses in 24 hours or as directed by doctor

adults and children 12 years of age and over | take 1 caplet every 4 hours as needed
children 6 to under 12 years of age | take ½ caplet every 4 hours as needed
children under 6 years of age | consult a doctor

Other information

- store at room temperature (15°-30°C)

Inactive ingredients

croscarmellose sodium, hypromellose, lactose, magnesium stearate, maltodextrin, microcrystalline celluclose, mineral oil, povidone, silicon dioxide, sodium lauryl sulfate, stearic acid, titanium dioxide, triacetin

Questions?

Adverse drug event call (866) 562-2756 Mon-Fri: 8 AM to 4 PM

PACKAGE LABEL

PHARBEST

NDC 16103-0389-04

Manufactured in the USA

Immediate Release

PHARBINEX-PE

Guaifenesin 400mg & Phenylephrine HCl 10mg

Expectorant & Nasal Decongestant

30 CAPLETS